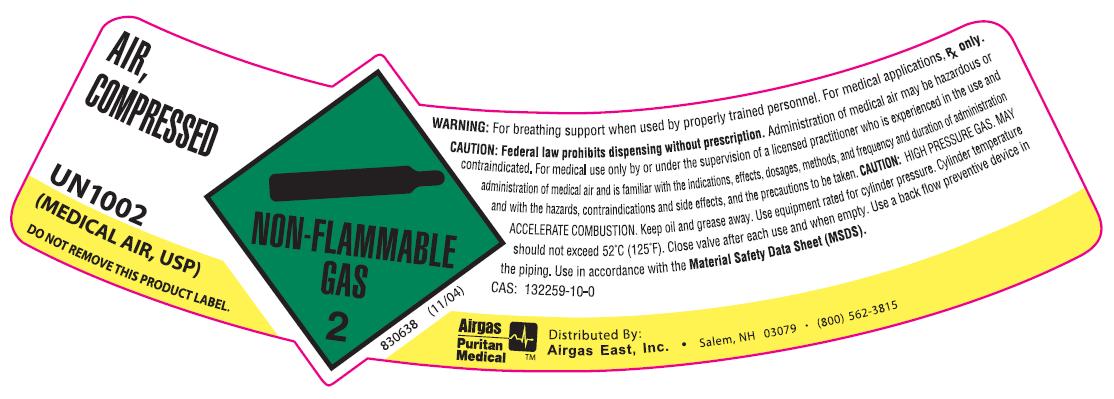 DRUG LABEL: Air
NDC: 25543-005 | Form: GAS
Manufacturer: Airgas East, Inc.
Category: prescription | Type: HUMAN PRESCRIPTION DRUG LABEL
Date: 20100527

ACTIVE INGREDIENTS: Air 1000 mL/1 L

air

PACKAGE LABEL

AIR, COMPRESSED UN1002
(MEDICAL AIR, USP)
DO NOT REMOVE THIS PRODUCT LABEL. NON-FLAMMABLE GAS 2 830638 (11/04)
WARNING: For breathing support when used by properly trained personnel. For medical applications, Rx only.
CAUTION: Federal law prohibits dispensing without prescription.
Administration of medical air may be hazardous or contraindicated. For medical use only by or under supervision of a licensed practitioner who is experienced in the use and administration of medical air and is familiar with the indications, effects, dosages, methods, and frequency and duration of administration, and with the hazards, contraindications, and side effects and the precautions to be taken. CAUTION: HIGH PRESSURE LIQUID AND GAS. MAY ACCELERATE COMBUSTION. Keep oil and grease away. Use equipment rated for cylinder pressure. Cylinder temperatures should not exceed 52C (125F). Close valve after each use and when empty. Use a back flow preventive device in the piping. Use in accordance with the Material Safety Data Sheet (MSDS). CAS: 132259-10-0
AIRGAS PURITAN MEDICAL AIRGAS EAST, Inc. Salem, NH 03079 (800) 562-3815